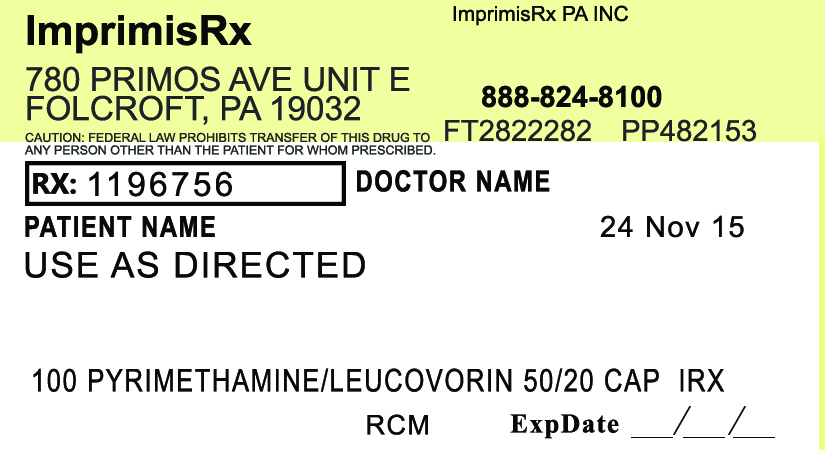 DRUG LABEL: Pyrimethamine Leucovorin
NDC: 70271-429 | Form: CAPSULE
Manufacturer: ImprimisRx PA, Inc. d/b/a ImprimisRx
Category: prescription | Type: HUMAN PRESCRIPTION DRUG LABEL
Date: 20151127

ACTIVE INGREDIENTS: PYRIMETHAMINE 50 mg/1 1; LEUCOVORIN CALCIUM 20 mg/1 1
INACTIVE INGREDIENTS: CELLULOSE, MICROCRYSTALLINE 70 mg/1 1

Pyrimethamine Leucovorin (50mg-20mg)